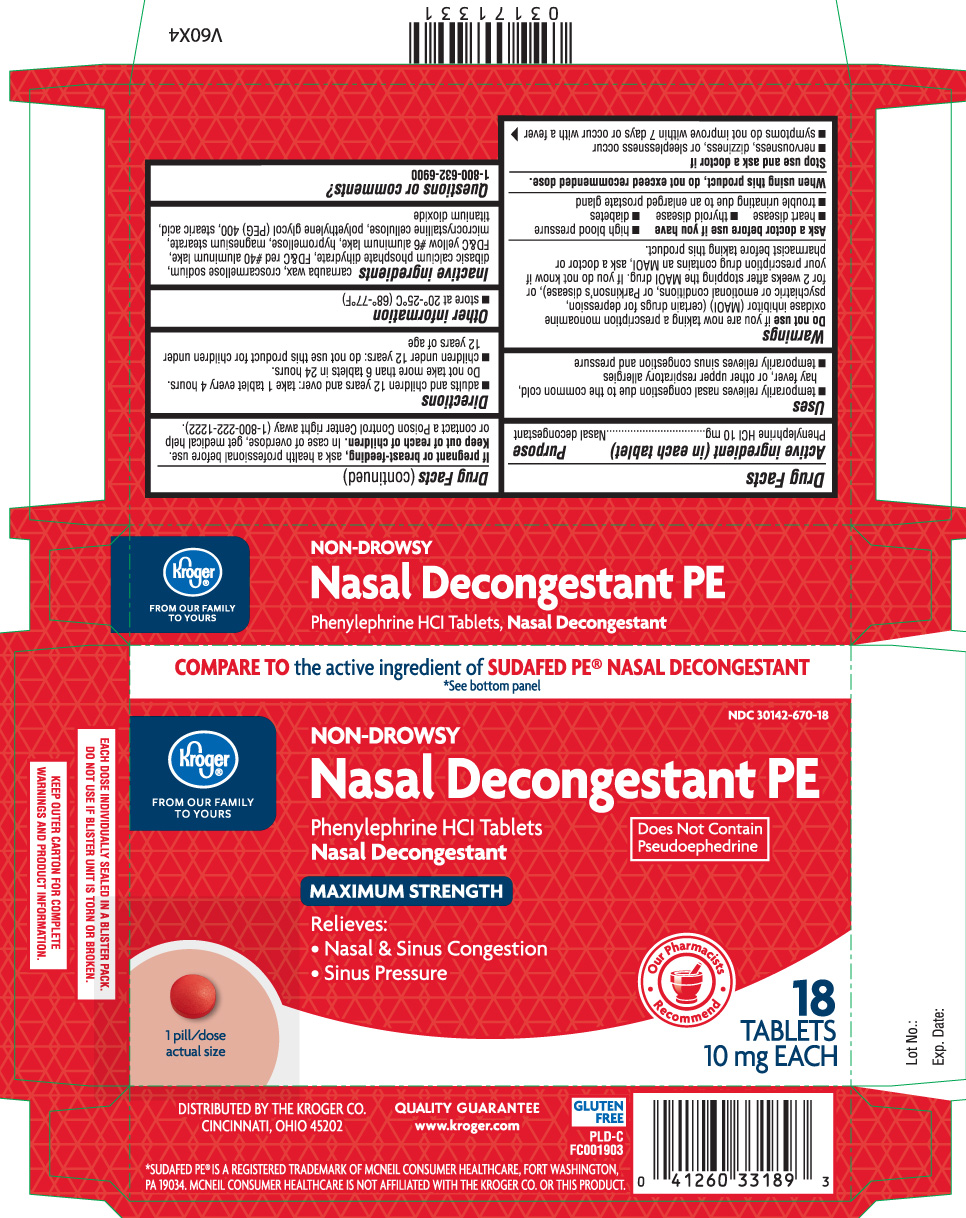 DRUG LABEL: Nasal Decongestant PE
NDC: 30142-670 | Form: TABLET
Manufacturer: The Kroger Co.
Category: otc | Type: HUMAN OTC DRUG LABEL
Date: 20140318

ACTIVE INGREDIENTS: PHENYLEPHRINE HYDROCHLORIDE 10 mg/1 1
INACTIVE INGREDIENTS: CARNAUBA WAX; CROSCARMELLOSE SODIUM; CALCIUM PHOSPHATE, DIBASIC, DIHYDRATE; FD&C RED NO. 40; FD&C YELLOW NO. 6; HYPROMELLOSES; MAGNESIUM STEARATE; CELLULOSE, MICROCRYSTALLINE; POLYETHYLENE GLYCOL 400; STEARIC ACID; TITANIUM DIOXIDE

Drug Facts

Active ingredient (in each tablet)

Phenylephrine HCl 10 mg

Purpose

Nasal decongestant

Uses

- temporarily relieves nasal congestion due to the common cold, hay fever, or other upper respiratory allergies
- temporarily relieves sinus congestion and pressure

Warnings

Do not use

if you are now taking a prescription monoamine oxidase inhibitor (MAOI) (certain drugs for depression, psychiatric or emotional conditions, or Parkinson’s disease), or for 2 weeks after stopping the MAOI drug. If you do not know if your prescription drug contains an MAOI, ask a doctor or pharmacist before taking this product.

Ask a doctor before use if you have

- high blood pressure
- heart disease
- thyroid disease
- diabetes
- trouble urinating due to an enlarged prostate gland

When using this product,

do not exceed recommended dose.

Stop use and ask a doctor if

- nervousness, dizziness, or sleeplessness occur
- symptoms do not improve within 7 days or occur with a fever

If pregnant or breast-feeding,

ask a health professional before use.

Keep out of reach of children.

In case of overdose, get medical help or contact a Poison Control Center right away (1-800-222-1222).

Directions

- adults and children 12 years and over: take 1 tablet every 4 hours. Do not take more than 6 tablets in 24 hours.
- children under 12 years: do not use this product for children under 12 years of age

Other information

- store at 20º-25ºC (68º-77ºF)

Inactive ingredients

carnauba wax, croscarmellose sodium, dibasic calcium phosphate dihydrate, FD&C red #40 aluminium lake, FD&C yellow #6 aluminium lake, hypromellose, magnesium stearate, microcrystalline cellulose, polyethylene glycol (PEG) 400, stearic acid, titanium dioxide

Questions or comments?

1-800-632-6900

Principal Display Panel

Compare to the active ingredient of SUDAFED PE® NASAL DECONGESTANT *See bottom panel

NON- DROWSY

Nasal Decongestant PE

Phenylephrine HCl Tablets

Nasal Decongestant

Does Not Contain Pseudoephedrine

MAXIMUM STRENGTH

Relieves:

- Nasal & Sinus Congestion
- Sinus Pressure

1 pill/dose

TABLETS 10 mg EACH

GLUTEN FREE

*Sudafed PE® is a registered trademark of McNeil Consumer Healthcare, Fort Washington, PA 19034. McNeil Consumer Healthcare is not affiliated with The Kroger Co. or this product.

EACH DOSE INDIVIDUALLY SEALED IN A BLISTER PACK . DO NOT USE IF BLISTER UNIT IS TORN OR BROKEN.

KEEP OUTER CARTON FOR COMPLETE WARNINGS AND PRODUCT INFORMATION.
Kroger Nasal Decongestant PE Tablets